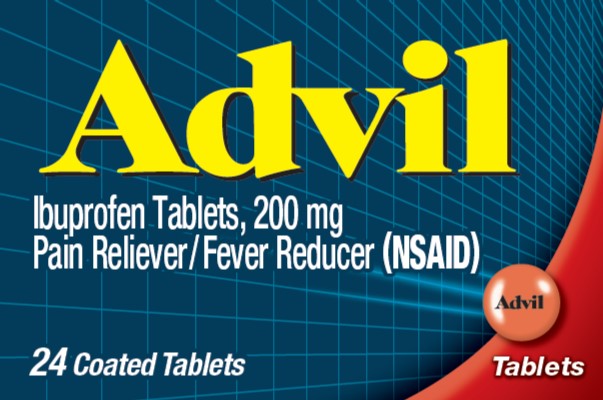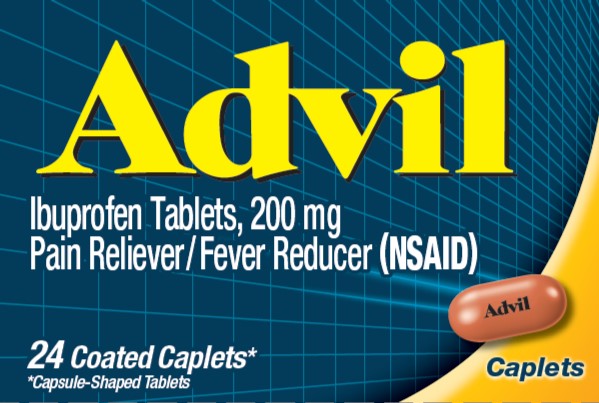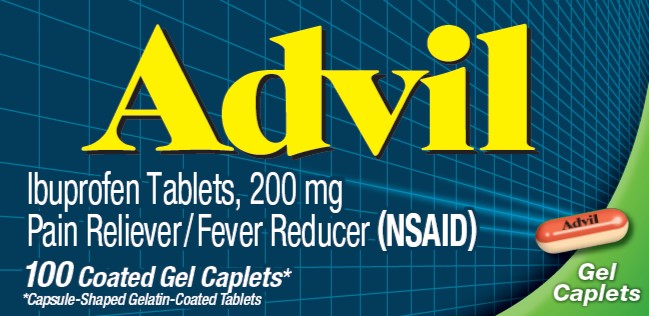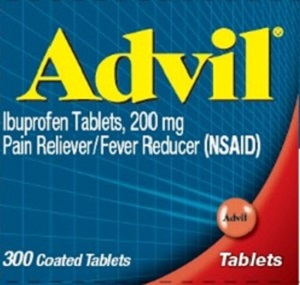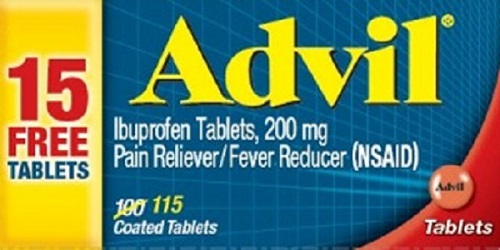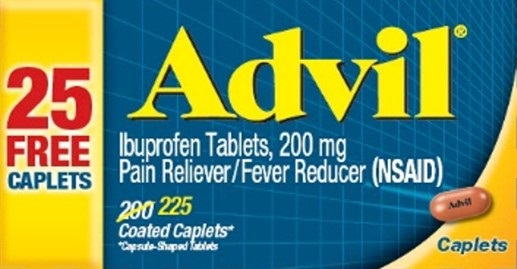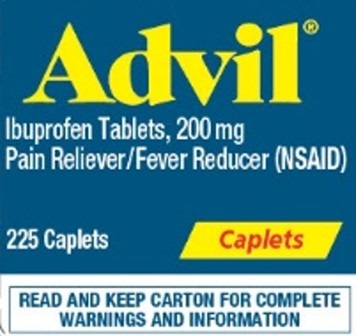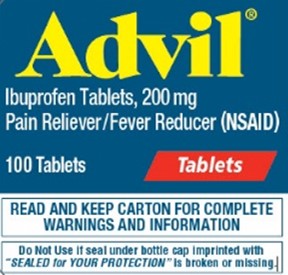 DRUG LABEL: ADVIL
NDC: 85237-1786 | Form: TABLET, COATED
Manufacturer: Select Consumer Group
Category: otc | Type: HUMAN OTC DRUG LABEL
Date: 20250818

ACTIVE INGREDIENTS: IBUPROFEN 200 mg/1 1
INACTIVE INGREDIENTS: MICROCRYSTALLINE CELLULOSE; CROSCARMELLOSE SODIUM; FERRIC OXIDE RED; METHYLPARABEN; POVIDONE, UNSPECIFIED; PROPYLPARABEN; SHELLAC; SILICON DIOXIDE; SODIUM BENZOATE; SODIUM LAURYL SULFATE; STARCH, CORN; STEARIC ACID; SUCROSE; TITANIUM DIOXIDE; WHITE WAX; DIACETYLATED MONOGLYCERIDES

Drug Facts

Active Ingredient

Advil Tablets (in each tablet)

Ibuprofen 200 mg (NSAID)*

*nonsteroidal anti-inflammatory drug

Advil Caplets (in each caplet)

Ibuprofen 200 mg (NSAID)*

*nonsteroidal anti-inflammatory drug

Advil Gel Caplets (in each gel caplet)

Ibuprofen 200 mg (NSAID)*

*nonsteroidal anti-inflammatory drug

Purpose

Pain reliever/Fever reducer

Uses

- temporarily relieves minor aches and pains due to:
  - headache
  - toothache
  - backache
  - menstrual cramps
  - the common cold
  - muscular aches
  - minor pain of arthritis
- temporarily reduces fever

Warnings

Allergy alert:

Ibuprofen may cause a severe allergic reaction, especially in people allergic to aspirin. Symptoms may include:

- hives
- facial swelling
- asthma (wheezing)
- shock
- skin reddening
- rash
- blisters

If an allergic reaction occurs, stop use and seek medical help right away.

Stomach bleeding warning:

This product contains an NSAID, which may cause severe stomach bleeding. The chance is higher if you

- are age 60 or older
- have had stomach ulcers or bleeding problems
- take a blood thinning (anticoagulant) or steroid drug
- take other drugs containing prescription or non-prescription NSAIDs [aspirin, ibuprofen, naproxen, or others]
- have 3 or more alcoholic drinks every day while using this product
- take more or for a longer time than directed

Heart attack and stroke warning:

NSAIDs, except aspirin, increase the risk of heart attack, heart failure, and stroke. These can be fatal. The risk is higher if you use more than directed or for longer than directed.

Do not use

- if you have ever had an allergic reaction to any other pain reliever/fever reducer
- right before or after heart surgery

Ask a doctor before use if

- stomach bleeding warning applies to you
- you have problems or serious side effects from taking pain relievers or fever reducers
- you have a history of stomach problems, such as heartburn
- you have high blood pressure, heart disease, liver cirrhosis, kidney disease, asthma, or had a stroke
- you are taking a diuretic

Ask a doctor or pharmacist before use if you are

- under a doctor's care for any serious condition
- taking aspirin for heart attack or stroke, because ibuprofen may decrease this benefit of aspirin
- taking any other drug

When using this product

- take with food or milk if stomach upset occurs

Stop use and ask a doctor if

- you experience any of the following signs of stomach bleeding:
  - feel faint
  - vomit blood
  - have bloody or black stools
  - have stomach pain that does not get better
- you have symptoms of heart problems or stroke:
  - chest pain
  - trouble breathing
  - weakness in one part or side of body
  - slurred speech
  - leg swelling
- pain gets worse or lasts more than 10 days
- fever gets worse or lasts more than 3 days
- redness or swelling is present in the painful area
- any new symptoms appear

If pregnant or breast-feeding,

ask a health professional before use. It is especially important not to use ibuprofen at 20 weeks or later in pregnancy unless definitely directed to do so by a doctor because it may cause problems in the unborn child or complications during delivery.

Keep out of reach of children.

In case of overdose, get medical help or contact a Poison Control Center right away.

Directions

Advil Tablets

- do not take more than directed
- the smallest effective dose should be used
- adults and children 12 years and over: take 1 tablet every 4 to 6 hours while symptoms persist
- if pain or fever does not respond to 1 tablet, 2 tablets may be used
- do not exceed 6 tablets in 24 hours, unless directed by a doctor
- children under 12 years: ask a doctor

Advil Caplets

- do not take more than directed
- the smallest effective dose should be used
- adults and children 12 years and over: take 1 caplet every 4 to 6 hours while symptoms persist
- if pain or fever does not respond to 1 caplet, 2 caplets may be used
- do not exceed 6 caplets in 24 hours, unless directed by a doctor
- children under 12 years: ask a doctor

Advil Gel Caplets

- do not take more than directed
- the smallest effective dose should be used
- adults and children 12 years and over: take 1 gel caplet every 4 to 6 hours while symptoms persist
- if pain or fever does not respond to 1 gel caplet, 2 gel caplets may be used
- do not exceed 6 gel caplets in 24 hours, unless directed by a doctor
- children under 12 years: ask a doctor

Other information

- read all warnings and directions before use. Keep carton.
- store at 20-25°C (68-77°F)
- avoid excessive heat above 40°C (104°F)

Inactive ingredients

Advil Tablets

acetylated monoglycerides, colloidal silicon dioxide, corn starch, croscarmellose sodium, methylparaben, microcrystalline cellulose, pharmaceutical glaze, pharmaceutical ink, povidone, pregelatinized starch, propylparaben, sodium benzoate, sodium lauryl sulfate, stearic acid, sucrose, synthetic iron oxide, titanium dioxide, white wax

Advil Caplets

acetylated monoglycerides, colloidal silicon dioxide, corn starch, croscarmellose sodium, methylparaben, microcrystalline cellulose, pharmaceutical glaze, pharmaceutical ink, povidone, pregelatinized starch, propylparaben, sodium benzoate, sodium lauryl sulfate, stearic acid, sucrose, synthetic iron oxide, titanium dioxide, white wax

Advil Gel Caplets

colloidal silicon dioxide, corn starch, croscarmellose sodium, FD&C red no. 40, FD&C yellow no. 6, fractionated coconut oil, gelatin, glycerin, hypromellose, pharmaceutical ink, pregelatinized starch, propyl gallate, purified water, sodium lauryl sulfate, stearic acid, synthetic iron oxides, titanium dioxide, triacetin

Questions or comments?

call toll free 1-800-88-ADVIL

PRINCIPAL DISPLAY PANEL – 100 Gel Caplet Bottle Carton

NDC 0573-0165-40

Advil

Ibuprofen Tablets, 200 mg
Pain Reliever / Fever Reducer (NSAID)

100 Coated Gel Caplets*
*Capsule-Shaped Gelatin-Coated Tablets

Gel
Caplets

000067202 Front Carton

PRINCIPAL DISPLAY PANEL - 300 Tablet Bottle Label

Advil®
Ibuprofen Tablets, 200 mg
Pain Reliever/Fever Reducer (NSAID)

300 Coated Tablets

Tablets

PRINCIPAL DISPLAY PANEL - 115 Tablet Bottle Carton

15
FREE
TABLETS

Advil®
Ibuprofen Tablets, 200 mg
Pain Reliever/Fever Reducer (NSAID)

115
Coated Tablets

Tablets

PRINCIPAL DISPLAY PANEL - 225 Caplet Bottle Carton

25
FREE
CAPLETS

Advil®
Ibuprofen Tablets, 200 mg
Pain Reliever/Fever Reducer (NSAID)

225
Coated Caplets*
*Capsule-Shaped Tablets

Caplets

PRINCIPAL DISPLAY PANEL - 24 Tablet Bottle Carton

NDC 0573-0150-20

Advil
Ibuprofen Tablets, 200 mg
Pain Reliever/Fever Reducer (NSAID)

24 Coated Tablets

Tablets

000067199 Front Carton

PRINCIPAL DISPLAY PANEL - 100 Tablet Bottle Label

Advil®
Ibuprofen Tablets, 200 mg
Pain Reliever/Fever Reducer (NSAID)

100 Tablets

Tablets

READ AND KEEP CARTON FOR COMPLETE
WARNINGS AND INFORMATION

Do Not Use if seal under bottle cap imprinted with
"SEALED for YOUR PROTECTION" is broken or missing.

PRINCIPAL DISPLAY PANEL - 24 Caplet Bottle Carton

NDC 0573-0160-20

Advil
Ibuprofen Tablets, 200 mg
Pain Reliever/Fever Reducer (NSAID)

24 Coated Caplets*
*Capsule-Shaped Tablets

Caplets

000067201 Front Carton

Principal Display Panel - 225 Caplet Bottle Label

NDC 0573-1711-14

Advil®
Ibuprofen Tablets, 200 mg
Pain Reliever/Fever Reducer (NSAID)

225 Caplets

Caplets

READ AND KEEP CARTON FOR COMPLETE
WARNINGS AND INFORMATION

PAA085439 Bottle Label